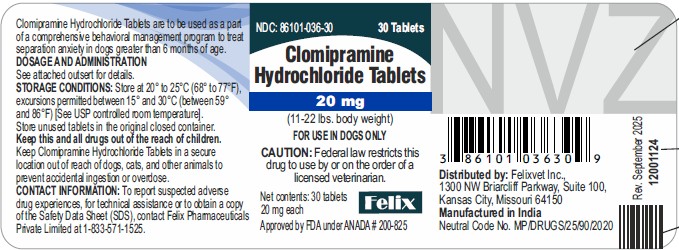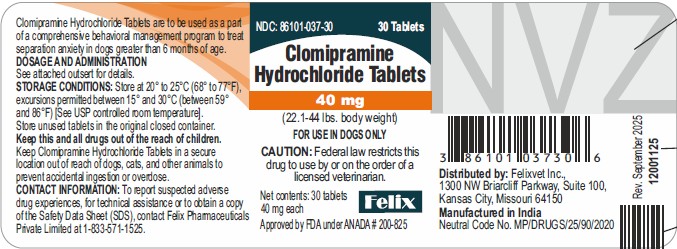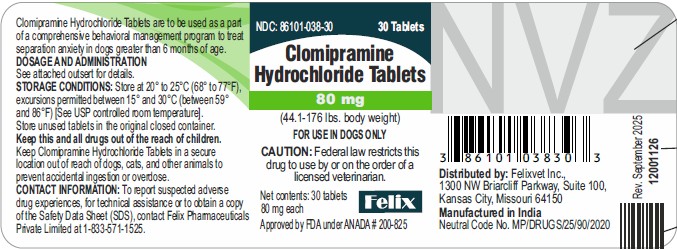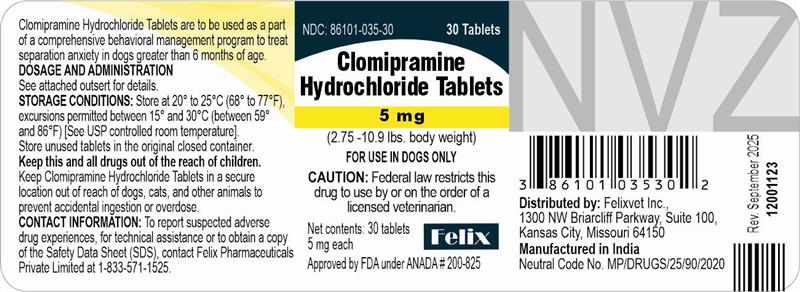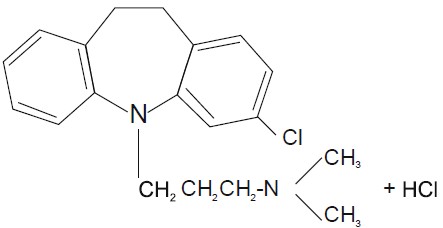 DRUG LABEL: Clomipramine Hydrochloride
NDC: 86101-035 | Form: TABLET
Manufacturer: FELIX PHARMACEUTICALS PRIVATE LIMITED
Category: animal | Type: Prescription Animal Drug Label
Date: 20251209

ACTIVE INGREDIENTS: CLOMIPRAMINE HYDROCHLORIDE 5 mg/1 1

Clomipramine Hydrochloride Tablets

Caution:

Federal law restricts this drug to use by or on the order of a licensed veterinarian.

Description:

Clomipramine Hydrochloride Tablets belong to the dibenzazepine class of tricyclic antidepressants. Clomipramine hydrochloride is 3-chloro-5[3-(dimethyl-amino)propyl]-10,11 dihydro-5H dibenz[b,f]azepine monohydrochloride. Clomipramine Hydrochloride Tablets are oblong, light brown in color and contain clomipramine hydrochloride formulated together with meat components. The molecular weight of clomipramine hydrochloride is 351.3. The structural formula is:

Clinical Pharmacology:

Clomipramine hydrochloride reduces the clinical signs of separation anxiety by affecting serotonergic and noradrenergic neuronal transmission in the central nervous system. While clomipramine hydrochloride can cause lethargy in dogs (see Adverse Reactions) its mode of action is not as a sedative. Clomipramine hydrochloride's capacity to inhibit re-uptake of serotonin in the central nervous system is believed to be the primary mechanism of action. Clomipramine hydrochloride is rapidly absorbed when administered orally. A single-dose crossover study involving 12 dogs evaluated clomipramine hydrochloride bioavailability after IV (2 mg/kg) and oral (4 mg/kg) administration in either a fed or fasted state. The administration of clomipramine hydrochloride in the presence of food resulted in an increase in the rate and extent of drug absorption as shown in the following table (mean ±SD):

 | AUC0-inf (nmol hr/L) | Cmax (nmol/L) | Tmax (hr) | Absolute Bioavailability (F)
Fed | 1670±575 | 601±286 | 1.18±0.32 | 0.21±0.07
Fasted | 1350±447 | 379±154 | 1.31±0.32 | 0.17±0.05

The absolute bioavailability is approximately 25% greater in fed dogs. The apparent terminal plasma half-life ranges from approximately 2 to 9 hours in fed and 3 to 21 hours in fasted dogs. The difference and variability in apparent half-life estimates may be attributable to prolonged drug absorption in the fasted state. The relatively large volume of distribution (3.8 ±0.8 L/kg) suggests that the drug is widely distributed throughout the body. Clomipramine is primarily metabolized in the liver.

Indications and Usage:

Clomipramine Hydrochloride Tablets are to be used as part of a comprehensive behavioral management program to treat separation anxiety in dogs greater than 6 months of age. Inappropriate barking or destructive behavior, as well as inappropriate elimination (urination or defecation) may be alleviated by the use of Clomipramine Hydrochloride Tablets in conjunction with behavior modification.

Separation anxiety is a complex behavior disorder displayed when the owner (or other attachment figure) leaves the dog. The signs of separation anxiety evaluated in controlled trials were vocalization, destructive behavior, excessive salivation, and inappropriate elimination. In the absence of the owner or attachment figure, dogs with separation anxiety may exhibit one or more of these clinical signs. Although the owner (attachment figure) may inadvertently misinterpret this behavior, which only happens in their absence, as spiteful, it is thought to be the result of anxiety experienced by the dog. Punishment is not considered appropriate for a dog with separation anxiety.

Proper recognition of clinical signs, including a complete patient history and assessment of the patient's household environment, is essential to accurately diagnose and treat separation anxiety.

The use of Clomipramine Hydrochloride Tablets should not replace appropriate behavioral and environmental management but should be used to facilitate a comprehensive behavior management program.

Contraindications:

Clomipramine Hydrochloride Tablets are contraindicated in dogs with known hypersensitivity to clomipramine or other tricyclic antidepressants.

Clomipramine Hydrochloride Tablets should not be used in male breeding dogs. Testicular hypoplasia was seen in dogs treated for 1 year at 12.5 times the maximum daily dose.

Clomipramine Hydrochloride Tablets should not be given in combination, or within 14 days before or after treatment with a monoamine oxidase inhibitor [e.g. selegiline hydrochloride (L-deprenyl),amitraz].

Clomipramine Hydrochloride Tablets are contraindicated for use in dogs with a history of seizures or concomitantly with drugs which lower the seizure threshold.

Human Warnings:

Not for use in humans. Keep out of reach of children. In case of accidental ingestion seek medical attention immediately. In children, accidental ingestion should be regarded as serious. There is no specific antidote for clomipramine. Overdose in humans causes anticholinergic effects including effects on the central nervous (e.g., convulsions) and cardiovascular (e.g., arrhythmia, tachycardia) systems. People with known hypersensitivity to clomipramine should administer the product with caution.

Keep Clomipramine Hydrochloride Tablets in a secure location out of reach of dogs, cats, and other animals to prevent accidental ingestion or overdose.

Precautions:

General: Clomipramine Hydrochloride Tablets are not recommended for other behavior problems, such as aggression (see Adverse Reactions). Studies to establish the safety and efficacy of clomipramine hydrochloride tablets in dogs less than 6 months of age have not been conducted.

Diagnosis: It is critical to conduct a comprehensive physical examination, including appropriate laboratory tests, and to obtain a thorough history and assessment of the patient's household environment, to rule-out causes of inappropriate behavior unrelated to separation anxiety before prescribing Clomipramine Hydrochloride Tablets. Periodic reassessment of hematological and serum biochemical data during the administration of this medication is advised. Veterinarians should be familiar with the risks and benefits of the treatment of behavioral disorders in dogs before initiating therapy. Inappropriate use of Clomipramine Hydrochloride Tablets, i.e., in the absence of a diagnosis or without concurrent behavioral modification, may expose the animal to unnecessary adverse effects and may not provide any lasting benefit of therapy.

Drug Interactions:

Recommendations on the interaction between clomipramine and other medications are extrapolated from data generated in humans. Plasma levels of tricyclic antidepressants have been reported to be decreased by the concomitant administration of hepatic enzyme inducers (e.g., barbiturates, phenytoin); therefore plasma concentrations of clomipramine may be decreased by the concomitant administration of phenobarbital. Plasma levels of closely related tricyclic antidepressants have been reported to be increased by the concomitant administration of hepatic enzyme inhibitors (e.g., cimetidine, fluoxetine). Tricyclic antidepressants themselves may exhibit hepatic enzyme inhibition and possibly increase plasma levels of barbiturates (phenobarbital). Caution is advised in using clomipramine with anticholinergic or sympathomimetic drugs or with other CNS-active drugs, including general anesthetics and neuroleptics.

Prior to elective surgery with general anesthetics, clomipramine should be discontinued for as long as clinically feasible.

Use in Concomitant Illness:

Use with caution in dogs with cardiovascular disease. At 20 mg/kg/day (5X the maximum recommended dose), bradycardia and arrhythmias (atrioventricular node block and ventricular extrasystole) were observed in dogs. Because of its anticholinergic properties, clomipramine should be used with caution in patients with increased intraocular pressure, a history of narrow angle glaucoma, urinary retention or reduced gastrointestinal motility. Because clomipramine is principally metabolized in the liver, caution is advised in using this medication in the presence of preexisting liver disease.

Reproductive Safety:

Safety studies to determine the effects of clomipramine hydrochloride tablets in pregnant or lactating female dogs have not been conducted. Clomipramine Hydrochloride Tablets should not be used in breeding males (see Contraindications).

Efficacy:

Dose Establishment: A 12 week, placebo-controlled, multi-site clinical trial was conducted in the US and Europe to establish an effective dose of clomipramine hydrochloride tablets in dogs. Treatment with clomipramine hydrochloride tablets, at 2 - 4 mg/kg/day divided twice daily, in conjunction with behavioral modification (desensitization and counterconditioning) was more effective than behavior modification alone in reducing the signs of separation anxiety in dogs.

Dose Confirmation: In another placebo-controlled, multi-site clinical trial, clomipramine hydrochloride tablets at 2 - 4 mg/kg/day given either once daily or divided twice daily showed significant improvement in resolving signs of separation anxiety when tested against behavioral modification alone (desensitization and counterconditioning). In this 8 week study, the rate of improvement of the dogs receiving clomipramine hydrochloride tablets with behavioral modification was significantly faster than the rate of improvement of the dogs receiving behavioral modification alone. After one week on trial, 47% of the dogs receiving clomipramine hydrochloride tablets once or twice (divided dose) daily in conjunction with behavioral modification showed clinical improvement compared to improvement in 29% of the dogs receiving behavioral modification alone.

Safety:

Clomipramine hydrochloride tablets were demonstrated to be well-tolerated in dogs at the recommended label dose of 2-4 mg/kg/day. In a six month target animal safety study, beagle dogs were dosed daily at 4 (1X), 12 (3X), and 20 (5X) mg/kg/day. Emesis was seen in all groups including the dogs receiving placebo, but occurred more frequently in dogs receiving 12 and 20 mg/kg. Decreased activity was also seen in dogs receiving the 12 and 20 mg/kg. There were no apparent treatment-related alterations in the following: body weights, physical examination findings, electrocardiograph examinations, hematology or biochemistry parameters, ophthalmoscopic examinations, macroscopic or microscopic organ examinations and organ weights. Average food and water consumption over the 26 week period was similar for control and treated groups. In a one year study, pure bred dogs were dosed daily at 12.5 (3X), 50 (12.5X), and 100 (25X) mg/kg/day. Emesis and mydriasis were observed within 15 minutes to one hour after dosing in dogs receiving 12.5, 50, and 100 mg/kg/day and lethargy was observed within 1 hour of dosing in dogs receiving 50 and 100 mg/kg. Testicular hypoplasia was seen in dogs receiving 50 mg/kg. At 100 mg/kg/day (25X) convulsions and eventual death occurred in five out of the eight dogs.

Adverse Reactions:

Frequency and category of adverse reactions observed in dogs dosed with clomipramine hydrochloride tablets or placebo were observed in multisite clinical studies as follows.

Adverse Reactions Reported in Placebo-Controlled Clinical Field Trials
 | Clomipramine Hydrochloride Tablets N=180 | Placebo N=88
Emesis | 36 (20%) | 8 (9%)
Lethargy | 26 (14%) | 7 (8%)
Diarrhea | 17 (9%) | 4 (5%)
Polydipsia | 6 (3%) | 0
Decreased Appetite | 6 (3%) | 3 (3%)
Aggression* | 3 (2%) | 1 (1%)
Seizure | 2 (1%) | 0
Dry Mouth | 1 (0.5%) | 1 (1%)
Tremors | 1 (0.5%) | 0
Constipation | 1 (0.5%) | 0
Anisocoria | 1 (0.5%) | 0
Polyuria | 1 (0.5%) | 0
Hyperthermia | 1 (0.5%) | 0

*These dogs displayed growling behavior towards either humans or other dogs.

Post-Approval Experience: Although not all adverse reactions are reported, the following adverse reactions are based on voluntary post-approval adverse drug experience reporting: lethargy/depression, anorexia, elevation in liver enzymes, vomiting and diarrhea. Hepatobiliary disease has occurred, especially in the presence of pre-existing conditions or with concurrent administration of drugs metabolized via the hepatic system. Additionally, in an overdose situation, the following signs have been reported: ataxia, convulsion(s), anticholinergic effects (e.g., mydriasis, bradycardia, tachycardia, and arrhythmia) and vocalization.

CONTACT INFORMATION:

To report suspected adverse drug experiences, for technical assistance or to obtain a copy of the Safety Data Sheet (SDS), contact Felix Pharmaceuticals Private Limited at 1-833-571-1525.

For additional information about adverse drug experience reporting for animal drugs, contact FDA at 1-888-FDA-VETS or http://www.fda.gov/reportanimalae

Dosage & Administration:

The recommended daily dose of Clomipramine Hydrochloride Tablets is 2 to 4 mg/kg/day (0.9 -1.8 mg/lb/day) (see dosing table below). It can be administered as a single daily dose or divided twice daily based on patient response and/or tolerance of the side effects. It may be prudent to initiate treatment in divided doses to minimize side effects by permitting tolerance to side effects to develop or allowing the patient time to adapt if tolerance does not develop. To reduce the incidence of vomiting that may be experienced by some dogs, Clomipramine Hydrochloride Tablets may be given with a small amount of food.

Dog Weight (lbs.) | Clomipramine Hydrochloride Tablets per Day | No. Tablets per Day | Tablet Strength
2.75-5.5 | 5 mg | 1 | 5 mg
5.6-10.9 | 10 mg | 2 | 5 mg
11-22 | 20 mg | 1 | 20 mg
22.1-44 | 40 mg | 1 | 40 mg
44.1-88 | 80 mg | 1 | 80 mg
88.1-176 | 160 mg | 2 | 80 mg

The specific methods of behavioral modification used in clinical trials involved desensitization and counterconditioning techniques. Since the manifestation of separation anxiety can vary according to the individual dog, it is advised that a specific behavior modification plan be developed based on a professional assessment of each individual case.

Once the desired clinical effect is achieved and the owners have successfully instituted the appropriate behavioral modification, the dose of Clomipramine Hydrochloride Tablets may be reduced to maintain the desired effect or discontinued. Withdrawal side effects were not reported in studies with clomipramine hydrochloride tablets in dogs. However, in clinical practice, it is recommended to taper the individual patient dose while continuing to monitor the dog's behavior and clinical status through the dose reduction or withdrawal period. Continued behavioral modification is recommended to prevent recurrence of the clinical signs.

The effectiveness and clinical safety of clomipramine hydrochloride tablets for long-term use (i.e., for more than 12 weeks) has not been evaluated.

Professional judgment should be used in monitoring the patient's clinical status, response to therapy and tolerance to side effects to determine the need to continue treatment with Clomipramine Hydrochloride Tablets and to continue to rule-out physiological disorders which may complicate the diagnosis and treatment of separation anxiety.

Storage Conditions:

Store at 20° to 25°C (68° to 77°F), excursions permitted between 15° and 30°C (between 59° and 86°F) [See USP controlled room temperature]. Store unused tablets in the original closed container.

How Supplied

NDC Number | Tablet Strength | Tablets/Bottle
86101-035-30 | 5 mg | 30
86101-036-30 | 20mg | 30
86101-037-30 | 40 mg | 30
86101-038-30 | 80 mg | 30

Clomipramine Hydrochloride Tablets are available in 5, 20, 40, and 80 mg tablet strengths in color-coded packaging for oral administration to dogs.

Keep this and all drugs out of reach of children.

Distributed by:

Felixvet Inc.,

1300 NW Briarcliff Parkway, Suite 100,

Kansas City, Missouri 64150

Manufactured in India

Neutral Code No. MP/DRUGS/25/90/2020

Rev. September 2025

Approved by FDA under ANADA # 200-825

Clomipramine Hydrochloride Tablets

Caution:
Federal law restricts this drug to use by or on the order of a licensed veterinarian.

Introduction:

Felix Pharmaceuticals Pvt Ltd., encourages you to take the time to read this package insert which describes the use of Clomipramine Hydrochloride Tablets for the treatment of separation anxiety in conjunction with behavior modification (training) in dogs. Clomipramine Hydrochloride Tablets do not act as a sedative. Instead, Clomipramine Hydrochloride Tablets help to reduce the anxiety associated with this condition, thus allowing your dog to more effectively benefit from behavior training. After reading this insert, if you have any questions about the use of Clomipramine Hydrochloride Tablets, please consult your veterinarian.

Description:
Clomipramine Hydrochloride Tablets belong to the dibenzazepine class of tricyclic antidepressants. Clomipramine hydrochloride is 3-chloro-5[3-(dimethylamino)propyl]-10,11 dihydro-5H dibenz[b,f]azepine monohydrochloride. Clomipramine Hydrochloride Tablets are oblong, light brown in color and contain clomipramine-hydrochloride formulated together with meat components.

Indications and Usage:

Clomipramine Hydrochloride Tablets are to be used as part of a comprehensive behavioral management program to treat separation anxiety in dogs greater than 6 months of age. Inappropriate barking or destructive behavior, as well as inappropriate elimination (urination or defecation) may be alleviated by the use of Clomipramine Hydrochloride Tablets in conjunction with behavior modification.

Separation anxiety is a complex behavior disorder displayed when the owner (or other attachment figure) leaves the dog. In the absence of the owner or attachment figure, dogs with separation anxiety may exhibit one or more clinical signs. The signs of separation anxiety evaluated in controlled trials were vocalization, destructive behavior, excessive salivation, and inappropriate elimination. Although it may appear that this behavior, which only happens in the dog owner's absence, is a spiteful action, this behavior is thought to be a result of anxiety experienced by the dog. Therefore, punishment would not be appropriate for the dog with this behavior.

Behavior Modification (Training):

Behavior training is a necessary component of therapy with Clomipramine Hydrochloride Tablets. In clinical trials, specific behavior training techniques were used at the following times:

- when the owner interacted with the dog while at home
- when the owner was preparing to leave the home
- when the owner returned home and greeted the dog

Since the methods used for behavior training can vary according to patient needs, it is important that you follow the instructions provided by your veterinarian regarding the specific techniques recommended for modifying your dog's behavior.

Contraindications:

Clomipramine Hydrochloride Tablets are contraindicated in dogs with known hypersensitivity to clomipramine or related tricyclic antidepressants. Clomipramine Hydrochloride Tablets should not be used in male breeding dogs. Testicular hypoplasia was seen in dogs treated for 1 year at 12.5 times the maximum daily dose.

Clomipramine Hydrochloride Tablets should not be given in combination, or within 14 days before or after treatment with a monoamine oxidase inhibitor [e.g. selegiline hydrochloride (L-deprenyl), amitraz].

Clomipramine Hydrochloride Tablets are contraindicated for use in dogs with a history of seizures or concomitantly with drugs which lower the seizure threshold.

Human Warnings:
Not for use in humans. KEEP OUT OF REACH OF CHILDREN. In case of accidental ingestion seek medical attention immediately. In children, accidental ingestion should be regarded as serious. There is no specific antidote for clomipramine. Overdose in humans causes anticholinergic effects including effects on the central nervous (e.g., convulsions) and cardiovascular (e.g., arrhythmia, tachycardia) systems. People with known hypersensitivity to clomipramine should administer the product with caution.

Keep Clomipramine Hydrochloride Tablets in a secure location out of reach of dogs, cats, and other animals to prevent accidental ingestion or overdose.

Precautions:

It is important that your dog be closely monitored by your veterinarian while on a treatment plan with Clomipramine Hydrochloride Tablets and behavior training. You must inform your veterinarian of any current or future medications you are administering to your dog. The use of Clomipramine Hydrochloride Tablets in conjunction with certain other drugs or when your dog has other illnesses may be contraindicated or increase the risks of adverse reactions.

It is important that you inform your veterinarian of any changes in your dog's environment including, but not limited to, a new family member, a new pet, a move to a new location, or a change in your existing daily schedule. Some changes may result in an altered response to therapy.

It is important to inform your veterinarian of any perceived changes in your dog's behavior, appetite, or overall health while administering any medication. Some dogs display a temporary lethargy with the first few days of clomipramine hydrochloride tablets treatment. In some cases, signs of separation anxiety, such as vocalization, may temporarily increase at the initiation of treatment. In an overdose situation, seek veterinary attention for your pet as soon as possible. The safety and efficacy of clomipramine hydrochloride tablets have not been established in dogs less than 6 months of age or in pregnant or lactating female dogs. Clomipramine Hydrochloride Tablets should not be used in breeding male dogs (see Contraindications). Clomipramine Hydrochloride Tablets are not recommended for other behavior problems, such as aggression.

Efficacy:
Clomipramine hydrochloride tablets were tested in clinical trials involving client-owned dogs to determine effectiveness. Clomipramine hydrochloride tablets, at 2 – 4 mg/kg/day (0.9 – 1.8 mg/pound/day) when used in conjunction with behavior training, accelerated both the time to improvement and the final result of separation anxiety therapy compared to behavioral training alone.

Adverse Reactions:
The following adverse reactions have been reported associated with administration of clomipramine hydrochloride tablets: lethargy/ depression, vomiting, diarrhea, elevation in liver enzymes, convulsion(s), increased heart rate, decreased heart rate, increased thirst and confusion. Liver disease has occurred, especially in the presence of pre-existing conditions or with concurrent administration of drugs metabolized by the liver. In overdoses, signs such as vomiting, lethargy or depression, weakness and incoordination, dilated pupils, and vocalization may occur. Consult with your veterinarian if your dog experiences these or any other conditions.

CONTACT INFORMATION:
To report suspected adverse drug experiences, for technical assistance or to obtain a copy of the Safety Data Sheet (SDS), contact Felix Pharmaceuticals Private Limited at 1-833-571-1525.

Dosage and Administration:
The recommended daily dose of Clomipramine Hydrochloride Tablets is 2 to 4 mg/kg/day (0.9 – 1.8 mg/lb/day) (see dosing table below). Your veterinarian will instruct you to give the drug either once a day or divide the daily dose into 2 separate doses depending on your dog's response to the drug or tolerance to any side effects. Clomipramine Hydrochloride Tablets may be given with a small amount of food in an attempt to reduce the incidence of vomiting that may be experienced by some dogs. If a dose is missed, the next dose should be administered (without doubling) at the next scheduled dosing time.

Dog Weight (lbs.) | Clomipramine Hydrochloride Tablets per Day | No. Tablets per Day | Tablet Strength
2.75-5.5 | 5 mg | 1 | 5 mg
5.6-10.9 | 10 mg | 2 | 5 mg
11-22 | 20 mg | 1 | 20 mg
22.1-44 | 40 mg | 1 | 40 mg
44.1-88 | 80 mg | 1 | 80 mg
88.1-176 | 160 mg | 2 | 80 mg

Your veterinarian may decrease the dose or discontinue treatment with Clomipramine Hydrochloride Tablets depending on your dog's response to treatment. Continued behavior training is recommended, even after cessation of drug therapy.

Storage Conditions:
Store at 20° to 25°C (68° to 77°F), excursions permitted between 15° and 30°C (between 59° and 86°F) [See USP controlled room temperature]. Store unused tablets in the original closed container.

How Supplied:

NDC Number | Tablet Strength | Tablets/Bottle
86101-035-30 | 5 mg | 30
86101-036-30 | 20mg | 30
86101-037-30 | 40 mg | 30
86101-038-30 | 80 mg | 30

Clomipramine Hydrochloride Tablets are available in 5, 20, 40 and 80 mg tablet strengths in color-coded packaging for oral administration to dogs.

KEEP THIS AND ALL DRUGS OUT OF REACH OF CHILDREN.

Distributed by:
Felixvet Inc.,
1300 NW Briarcliff Parkway, Suite 100,
Kansas City, Missouri 64150

Manufactured in India

Neutral Code No. MP/DRUGS/25/90/2020

Rev. September 2025

Approved by FDA under ANADA # 200-825

PACKAGE LABEL.PRINCIPAL DISPLAY PANEL

NDC: 86101-035-30 30 Tablets

Clomipramine Hydrochloride Tablets

5 mg

(2.75 -10.9 lbs. body weight)

FOR USE IN DOGS ONLY

CAUTION: Federal law restricts this drug to use by or on the order of a licensed veterinarian.

Net contents: 30 tablets

5 mg each

Approved by FDA under ANADA # 200-825

PACKAGE LABEL.PRINCIPAL DISPLAY PANEL

NDC: 86101-036-30 30 Tablets

Clomipramine Hydrochloride Tablets

20 mg

(11-22 lbs. body weight)

FOR USE IN DOGS ONLY

CAUTION: Federal law restricts this drug to use by or on the order of a licensed veterinarian.

Net contents: 30 tablets

20 mg each

Approved by FDA under ANADA # 200-825

PACKAGE LABEL.PRINCIPAL DISPLAY PANEL

NDC: 86101-037-30 30 Tablets

Clomipramine Hydrochloride Tablets

40 mg

(22.1-44 lbs. body weight)

FOR USE IN DOGS ONLY

CAUTION: Federal law restricts this drug to use by or on the order of a licensed veterinarian.

Net contents: 30 tablets

40 mg each

Approved by FDA under ANADA # 200-825

PACKAGE LABEL.PRINCIPAL DISPLAY PANEL

NDC: 86101-038-30 30 Tablets

Clomipramine Hydrochloride Tablets

80 mg

(44.1-176 lbs. body weight)

FOR USE IN DOGS ONLY

CAUTION: Federal law restricts this drug to use by or on the order of a licensed veterinarian.

Net contents: 30 tablets

80 mg each

Approved by FDA under ANADA # 200-825